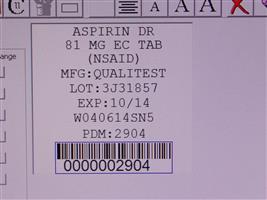 DRUG LABEL: Aspirin
NDC: 68151-2904 | Form: TABLET
Manufacturer: Carilion Materials Management
Category: otc | Type: HUMAN OTC DRUG LABEL
Date: 20180206

ACTIVE INGREDIENTS: ASPIRIN 81 mg/1 1
INACTIVE INGREDIENTS: CARNAUBA WAX; ANHYDROUS LACTOSE; SILICON DIOXIDE; CROSCARMELLOSE SODIUM; D&C YELLOW NO. 10; POLYSORBATE 80; SODIUM HYDROXIDE; TALC; TITANIUM DIOXIDE; TRIETHYL CITRATE; METHACRYLIC ACID - ETHYL ACRYLATE COPOLYMER (1:1) TYPE A; DIMETHICONE; FERRIC OXIDE RED

Aspirin

ACTIVE INGREDIENTS (IN EACH TABLET)

Aspirin 81mg (NSAID*)

*nonsteroidal anti-inflammatory drug

PURPOSE

Pain reliever

USES

for the temporary relief of minor aches and pains or as recommended by your doctor. Because of its delayed action, this product will not provide fast relief of headaches or other symptoms needing immediate relief.

WARNINGS

Reye's syndrome: Children and teenagers who have or are recovering from chicken pox or flu-like symptoms should not use this product. When using this product, if changes in behavior with nausea and vomiting occur, consult a doctor because these symptoms could be an early sign of Reye's syndrome, a rare but very serious illness.

Allergy alert: Aspirin may cause a severe allergic reaction which may include:

- hives
- facial swelling
- asthma (wheezing)
- shock

if an allergic reaction occurs, stop use and seek medical help right away.

Stomach bleeding warning: This product contains an NSAID, which may cause severe stomach bleeding. The chance is higher if you

- are age 60 or older
- have had stomach ulcers or bleeding problems
- take a blood thinning (anticoagulant) or steroid drug
- take other drugs containing prescription or nonprescription NSAIDs (aspirin, ibuprofen, naproxen, or others)
- have 3 or more alcoholic drinks every day while using this product
- take more or for a longer time than directed

Do not Use

if you are allergic to aspirin or other pain relievers/fever reducers

Ask a doctor before use if

- stomach bleeding warning applies to you
- you have a history of stomach problems, such as heartburn
- you have high blood pressure, heart disease, liver cirrhosis, or kidney disease
- you have asthma
- you are taking a diuretic

Ask a doctor or pharmacist before use if you are

Taking a prescription drug for:

- anticoagulation (thinning of the blood)
- diabetes
- gout
- arthritis

Stop use and ask a doctor if

- you experience any of the following signs of stomach bleeding: feel faint, vomit blood, have bloody or black stools, have stomach pain that does not get better
- new symptoms occur
- redness or swelling is present
- Ringing in the ears or loss of hearing occurs
- Pain gets worse or lasts for more than 10 days

If pregnant or breast-feeding,

ask a health professional before use. It is especially important not to use aspirin during the last 3 months of pregnancy unless specifically directed to do so by a doctor because it may cause problems in the unborn child or complications during delivery.

Keep out of reach of children.

In case of overdose, get medical help or contact a Poison Control Center right away.

DIRECTIONS

- drink a full glass of water with each dose
- adults and children 12 years and over: take 4 to 8 tablets every 4 hours not to exceed 48 tablets in 24 hours unless directed by a doctor
- children under 12 years: consult a doctor

OTHER INFORMATION

- store at room temperature
- do not use if imprinted safety seal under cap is broken or missing

You may report side effects to: 1-888-952-0050.

INACTIVE INGREDIENTS

anhydrous lactose, carnauba wax, croscarmlellose sodium, D&C yellow #10 aluminum lake, iron oxide ochre, methacrylic acid copolymer, microcrystalline cellulose, polysorbate 80, silicon dioxide, simethicone, sodium hydroxide, sodium lauryl sulfate, talc, titanium dioxide, triethyl citrate

HOW SUPPLIED

Product: 68151-2904

NDC: 68151-2904-2 1 TABLET in a PACKAGE